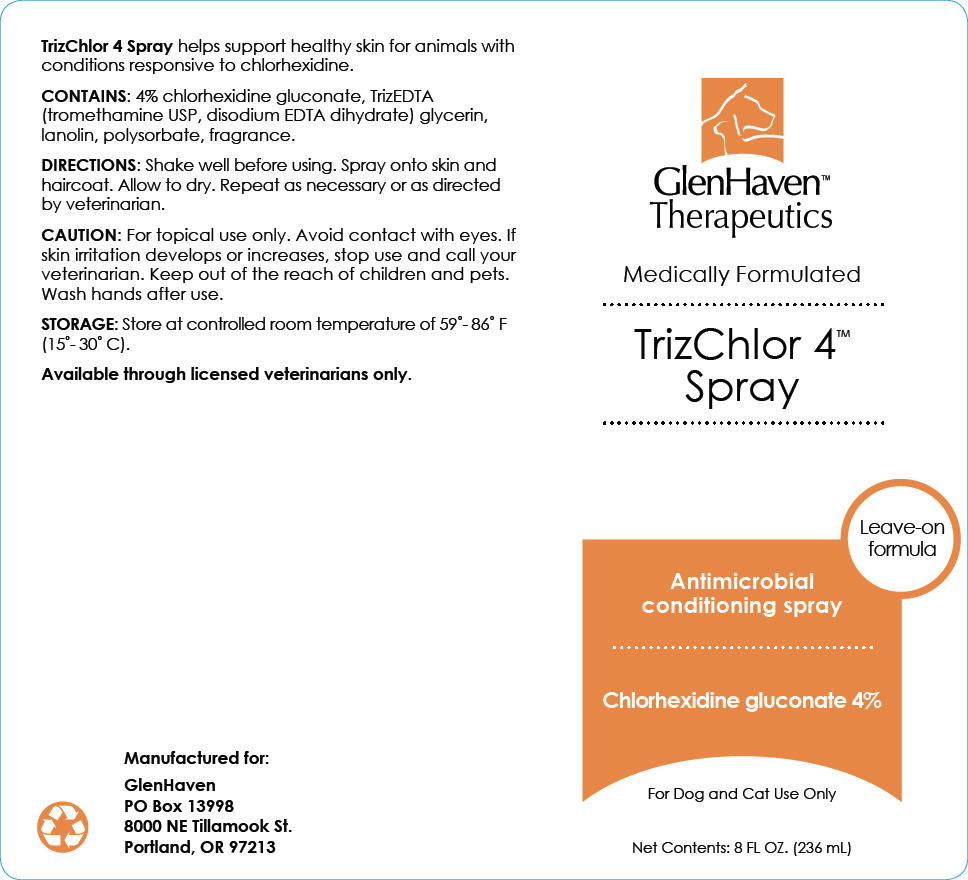 DRUG LABEL: Glen Haven TrizChlor 4
NDC: 70782-258 | Form: SOLUTION
Manufacturer: GlenHaven LLC
Category: animal | Type: OTC ANIMAL DRUG LABEL
Date: 20211208

ACTIVE INGREDIENTS: Chlorhexidine Gluconate 4 mg/1 mL

TrizChlor 4™ Spray

VETERINARY INDICATIONS

TrizChlor 4 Spray helps support healthy skin for animals with conditions responsive to chlorhexidine.

DESCRIPTION

CONTAINS: 4% chlorhexidine gluconate, TrizEDTA (tromethamine USP, disodium EDTA dihydrate) glycerin, lanolin, polysorbate, fragrance.

DOSAGE AND ADMINISTRATION

DIRECTIONS: Shake well before using. Spray onto skin and haircoat. Allow to dry. Repeat as necessary or as directed by veterinarian.

SAFE HANDLING WARNING

CAUTION: For topical use only. Avoid contact with eyes. If skin irritation develops or increases, stop use and call your veterinarian. Keep out of the reach of children and pets. Wash hands after use.

HOW SUPPLIED

STORAGE AND HANDLING

STORAGE: Store at controlled room temperature of 59˚-86˚ F (15˚- 30˚ C).

Available through licensed veterinarians only.

Manufactured for:

GlenHaven
PO Box 13998
8000 NE Tillamook St.
Portland, OR 97213

PRINCIPAL DISPLAY PANEL - 236 mL Bottle Label

GlenHaven™
Therapeutics

Medically Formulated

TrizChlor 4™
Spray

Leave-on
formula

Antimicrobial
conditioning spray

Chlorhexidine gluconate 4%

For Dog and Cat Use Only

Net Contents: 8 FL OZ. (236 mL)